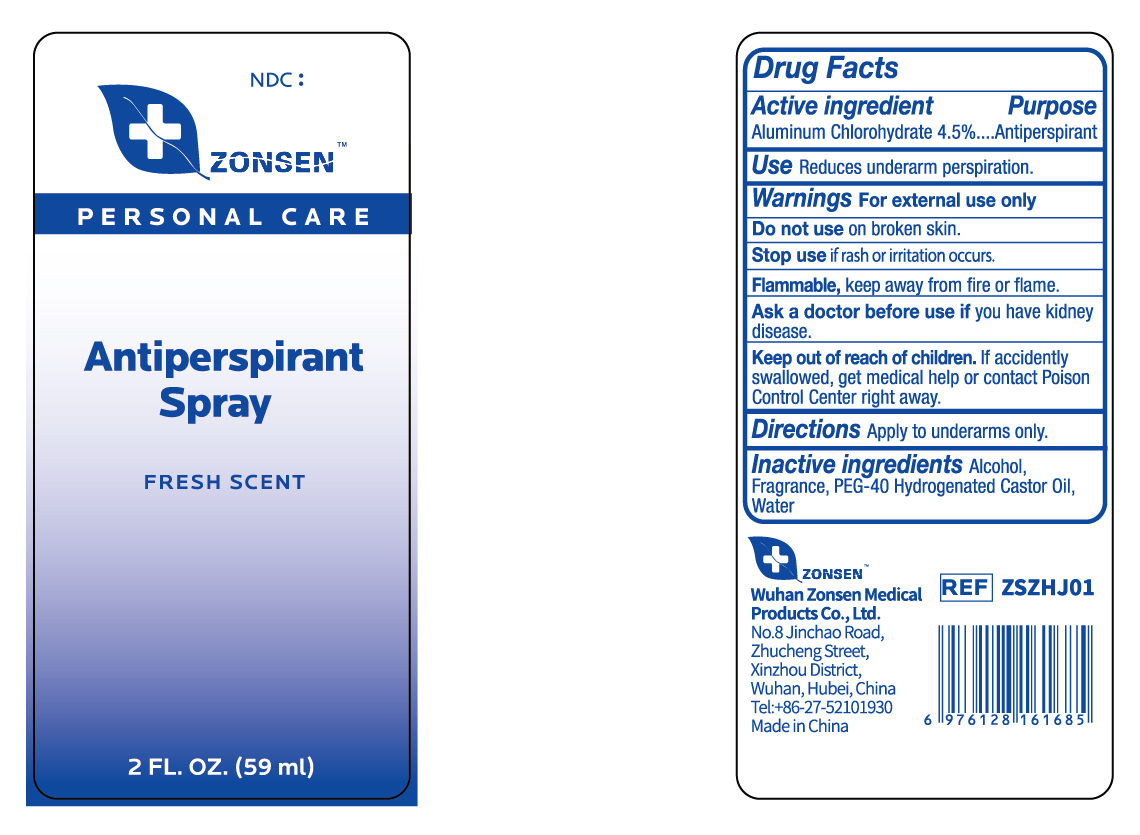 DRUG LABEL: ZONSEN Antiperspirant
NDC: 72932-010 | Form: LIQUID
Manufacturer: Wuhan Zonsen Medical Products Co., Ltd.
Category: otc | Type: HUMAN OTC DRUG LABEL
Date: 20240815

ACTIVE INGREDIENTS: ALUMINUM CHLOROHYDRATE 45 mg/1 mL
INACTIVE INGREDIENTS: POLYOXYL 40 HYDROGENATED CASTOR OIL; ALCOHOL 95%; WATER

ACTIVE INGREDIENT

Aluminum Chlorohydrate 4.5%

PURPOSE

Antiperspirant

Use

Reduces underarm perspiration.

Warnings

For external use only.

DO NOT USE

on broken skin.

STOP USE

if rash or irritation occurs.

ASK DOCTOR BEFORE USE

if you have kidney disease.

FLAMMABLE

Keep away from fire or flame.

KEEP OUT OF REACH OF CHILDREN

If accidently swallowed, get medical help or contact Poison Control Center right away

DIRECTIONS

Apply to underarms only.

INACTIVE INGREDIENTS

Water, Alcohol , PEG-40 Hydrogenated Castor Oil, Fragrance

DOSAGE & ADMINISTRATION

Use daily for best results.

PACKAGE LABEL

ZONSEN

PERSONAL CARE

Antiperspirant Spray

FRESH SCENT

2 FL. OZ. (59ml)